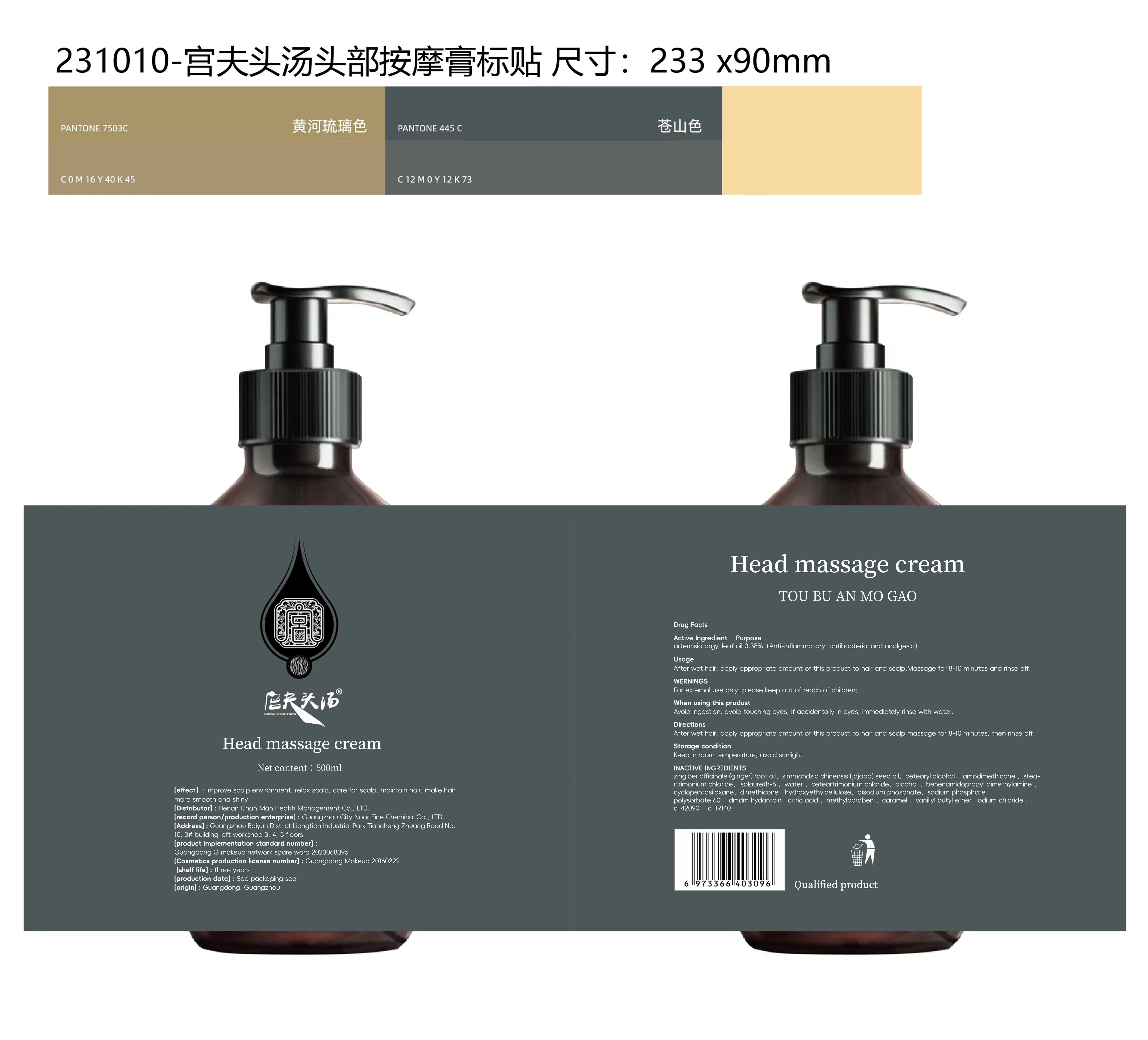 DRUG LABEL: GONGFUTOUTANG Head massage cream
NDC: 84286-004 | Form: CREAM
Manufacturer: Henan Chanman Health Management Co., Ltd
Category: otc | Type: HUMAN OTC DRUG LABEL
Date: 20240507

ACTIVE INGREDIENTS: ARTEMISIA ARGYI LEAF 0.38 g/100 mL
INACTIVE INGREDIENTS: BEHENAMIDOPROPYL DIMETHYLAMINE; SODIUM PHOSPHATE, DIBASIC, ANHYDROUS; SODIUM PHOSPHATE; FD&C BLUE NO. 1; CETOSTEARYL ALCOHOL; DMDM HYDANTOIN; ACONITIC ACID; WATER; METHYLPARABEN; VANILLYL BUTYL ETHER; CARAMEL; GINGER OIL; AMODIMETHICONE (1300 CST); CYCLOMETHICONE 5; TRIMETHYL OCTADECYL AMMONIUM CHLORIDE; JOJOBA OIL; ISOLAURETH-6; CETEARTRIMONIUM CHLORIDE; ALCOHOL; DIMETHICONE; HYDROXYETHYL CELLULOSE, UNSPECIFIED; POLYSORBATE 60; SODIUM CHLORIDE; FD&C YELLOW NO. 5

84286-004

Active Ingredient

artemisia argyi leaf oil 0.38%

Purpose

Anti-inflammatory, antibacterial and analgesic

Use

After wet hair, apply appropriate amount of this product to hair and scalp.Massage for 8-10 minutes and rinse off.

Warnings

For external use only, please keep out of reach of children

When Using

After wet hair, apply appropriate amount of this product to hair and scalp.Massage for 8-10 minutes and rinse off.

Keep Oot Of Reach Of Children

please keep out of reach of children

Directions

After wet hair, apply appropriate amount of this product to hair and scalp massage for 8-10 minutes, then rinse off.

Other information

Keep in room temperature, avoid sunlight

Inactive ingredients

Water
zingiber officinale (ginger) root oil
simmondsia chinensis (jojoba) seed oil
cetearyl alcohol
amodimethicone
steartrimonium chloride
isolaureth-6
ceteartrimonium chloride
alcohol
behenamidopropyl dimethylamine
cyclopentasiloxane
dimethicone
hydroxyethylcellulose
disodium phosphate
sodium phosphate
polysorbate 60
dmdm hydantoin
citric acid
methylparaben
caramel
vanillyl butyl ether
odium chloride
ci 42090
ci 19140